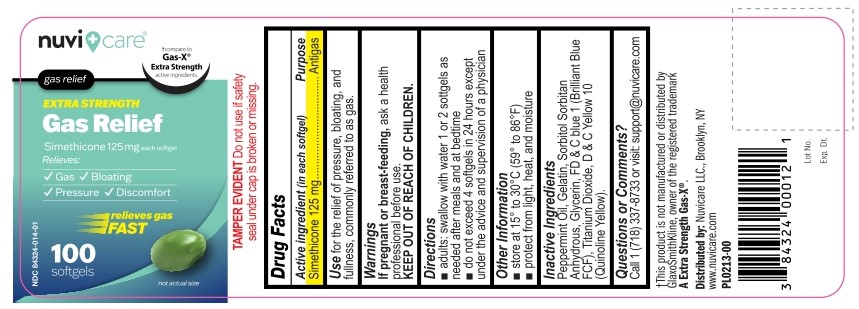 DRUG LABEL: Gas Relief Simethicone 125mg Softgel
NDC: 84324-014 | Form: CAPSULE, LIQUID FILLED
Manufacturer: NUVICARE LLC
Category: otc | Type: HUMAN OTC DRUG LABEL
Date: 20251219

ACTIVE INGREDIENTS: DIMETHICONE 125 mg/1 1
INACTIVE INGREDIENTS: PEPPERMINT OIL; GELATIN; SORBITOL; SORBITAN; GLYCERIN; FD&C BLUE NO. 1; TITANIUM DIOXIDE; D&C YELLOW NO. 10

Gas Relief Simethicone 125mg Softgel

Active Ingredient (in each softgel)

Simethicone 125 mg

Purpose

Antigas

Use

Use for the relief of pressure, bloating, and fullness, commonly referred to as gas.

Warnings

If pregnant or breast-feeding, ask a health professional before use.

KEEP OUT OF REACH OF CHILDREN.

Directions

- adults: swallow with water 1 or 2 softgels as needed after meals and at bedtime
- do not exceed 4 softgels in 24 hours except under the advice and supervision of a physician

Other Information

- store at 15° to 30°C (59° to 86°F)
- protect from light, heat, and moisture

Inactive Ingredients

Peppermint Oil, Gelatin, Sorbitol, Sorbitan Anhydrous, Glycerin, FD & C blue 1 (Brilliant Blue FCF), Titanium Dioxide, D & C Yellow 10 (Quinoline Yellow).

Questions or Comments?

Call 1 (718) 337-8733 or visit support@nuvicare.com